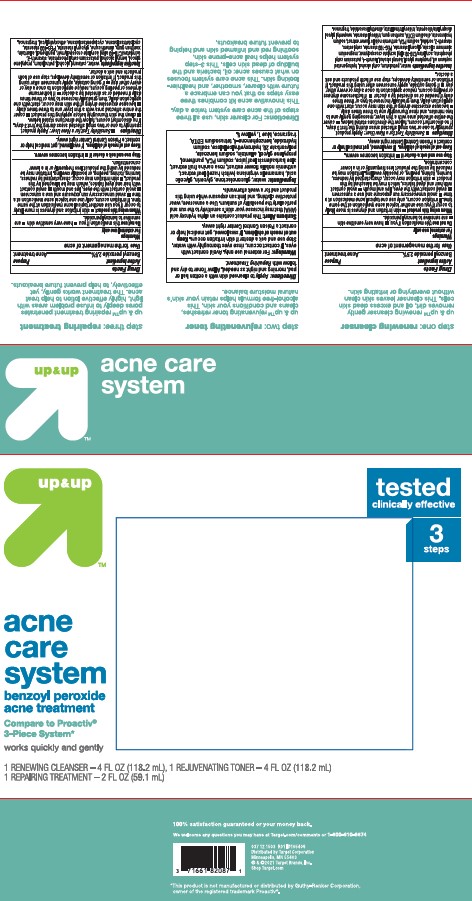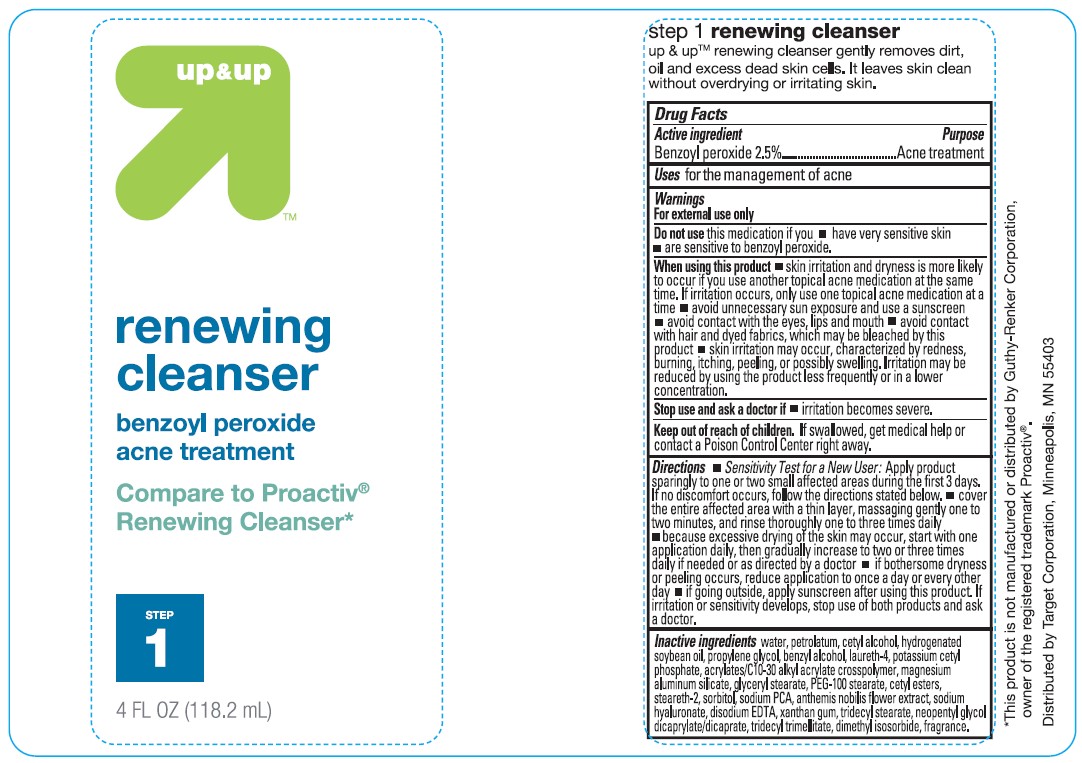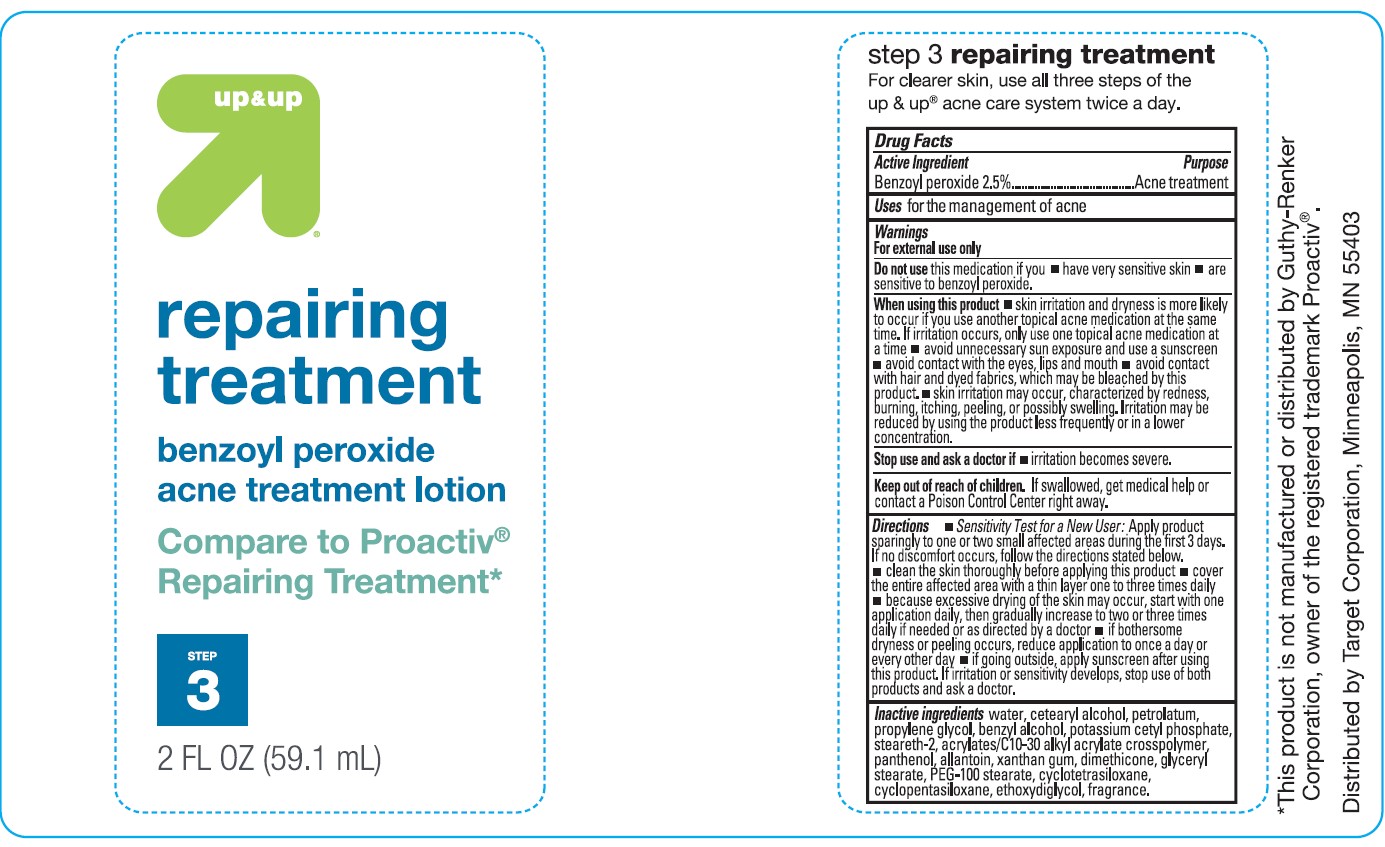 DRUG LABEL: Target Up and Up 3 Step Acne System
NDC: 11673-152 | Form: KIT | Route: TOPICAL
Manufacturer: TARGET CORPORATION
Category: otc | Type: HUMAN OTC DRUG LABEL
Date: 20241014

ACTIVE INGREDIENTS: BENZOYL PEROXIDE 2.5 g/100 mL; BENZOYL PEROXIDE 2.5 g/100 mL
INACTIVE INGREDIENTS: STEARETH-2; POTASSIUM CETYL PHOSPHATE; GLYCERYL MONOSTEARATE; HYDROGENATED SOYBEAN OIL; WATER; MAGNESIUM ALUMINUM SILICATE; PEG-100 STEARATE; SORBITOL; DIMETHYL ISOSORBIDE; TRIDECYL STEARATE; NEOPENTYL GLYCOL DICAPRYLATE/DICAPRATE; CETYL ESTERS WAX; CHAMAEMELUM NOBILE FLOWER; HYALURONATE SODIUM; SODIUM PYRROLIDONE CARBOXYLATE; XANTHAN GUM; TRIDECYL TRIMELLITATE; PROPYLENE GLYCOL; EDETATE DISODIUM; CARBOMER COPOLYMER TYPE B (ALLYL PENTAERYTHRITOL CROSSLINKED); CETYL ALCOHOL; PETROLATUM; LAURETH-4; BENZYL ALCOHOL; CARBOMER COPOLYMER TYPE B (ALLYL PENTAERYTHRITOL CROSSLINKED); BENZYL ALCOHOL; PETROLATUM; STEARETH-2; WATER; DIETHYLENE GLYCOL MONOETHYL ETHER; CYCLOMETHICONE 4; CYCLOMETHICONE 5; CETOSTEARYL ALCOHOL; PROPYLENE GLYCOL; DIMETHICONE; GLYCERYL MONOSTEARATE; PEG-100 STEARATE; PANTHENOL; ALLANTOIN; XANTHAN GUM; POTASSIUM CETYL PHOSPHATE

Target Up and Up 3 Step Acne System

Active ingredient

Benzoyl Peroxide 2.5%

Purpose

Acne Treatment

Uses

for the management of acne

Warnings

For external use only.

Do not use if you

- have very sensitive skin
- are sensitive to benzoyl peroxide.

When using this product

• skin irritation and dryness is more likely to occur if you use another topical acne medication at the same time. If irritation occurs, only use one topical acne medication at a time. • avoid unnecessary sun exposure and use a sunscreen • avoid contact with eyes, lips, and mouth • avoid contact with hair and dyed fabrics, which may be bleached by this product • skin irritation may occur, characterized by redness, burning, itching, peeling, or possibly swelling. Irritation may be reduced by using the product less frequently or in a lower concentration.

Stop use and ask a doctor if

- irritation becomes severe.

Keep out of reach of the children

If product is swallowed, get medical help or contact a Poison Control Center right away

Directions

- Sensitivity Test for a New User: Apply product sparingly to one or two small affected areas during the first 3 days. If no discomfort occurs, follow the directions stated below.
- cover the entire affected area with a thin layer, massaging gently one to two minutes, and rinse thoroughly one to three times daily
- because excessive drying of the skin may occur, start with one application daily, then gradually increase to two to three times daily if needed or as directed by a doctor
- if bothersome dryness or peeling occurs, reduce application to once a day or every other day
- if going outside, apply sunscreen after using this product. If irritation or sensitivity develops, stop use of both products and ask a doctor.

Inactive ingredients

WATER, PETROLATUM, CETYL ALCOHOL, HYDROGENATED SOYBEAN OIL, PROPYLENE GLYCOL, BENZYL ALCOHOL, LAURETH-4, POTASSIUM CETYL PHOSPHATE, ACRYLATES/C10-30 ALKYL ACRYLATE CROSSPOLYMER, MAGNESIUM ALUMINUM SILICATE, GLYCERYL STEARATE, PEG-100 STEARATE, CETYL ESTERS, STEARETH-2, SORBITOL, SODIUM PCA, ANTHEMIS NOBILIS FLOWER EXTRACT, SODIUM HYALURONATE, DISODIUM EDTA, XANTHAN GUM, TRIDECYL STEARATE, NEOPENTYL GLYCOL DICAPRYLATE/DICAPRATE, TRIDECYL TRIMELLITATE, DIMETHYL ISOSORBIDE, FRAGRANCE.

Active ingredient

Benzoyl Peroxide 2.5%

Purpose

Acne Treatment

Uses

for the management of acne

Warnings

For external use only.

Do not use this medication if you

- have very sensitive skin
- are sensitive to benzoyl peroxide.

When using this product

• skin irritation and dryness is more likely to occur if you use another topical acne medication at the same time. If irritation occurs, only use one topical acne medication at a time. • avoid unnecessary sun exposure and use a sunscreen •avoid contact with eyes, lips, and mouth • avoid contact with hair and dyed fabrics, which may be bleached by this product • skin irritation may occurs, characterized by redness, burning, itching, peeling, or possibly swelling. Irritation may be reduced by using the product less frequently or in a lower concentration.

Stop use and ask a doctor if

- irritation becomes severe.

Keep out of reach of the children

If product is swallowed, get medical help or contact a Poison Control Center right away

Directions

•Sensitivity Test for a New User: Apply product sparingly to one or two small affected areas during the first 3 days. If no discomfort occurs, follow the directions stated below.

- cleanthe skin thoroughly before applying this product
- cover the entire affected area with a thin layer one to three times daily
- because excessive drying of the skin may occur, start with one application daily, then gradually increase to two to three times daily if needed or as directed by a doctor
- if bothersome dryness or peeling occurs, reduce application to once a day or every other day
- if going outside, apply sunscreen after using this product. If irritation or sensitivity develops, stop use of both products and ask a doctor.

Inactive ingredients

WATER, CETEARYL ALCOHOL, PETROLATUM, BENZYL ALCOHOL, POTASSIUM CETYL PHOSPHATE, STEARETH-2, ACRYLATES/C10-30 ALKYL ACRYLATE CROSSPOLYMER, PANTHENOL, ALLANTOIN, PROPYLENE GLYCOL, XANTHAN GUM, DIMETHICONE, GLYCERYL STEARATE, PEG-100 STEARATE, CYCLOTETRASILOXANE, CYCLOPENTASILOXANE, ETHOXYDIGLYCOL, FRAGRANCE.